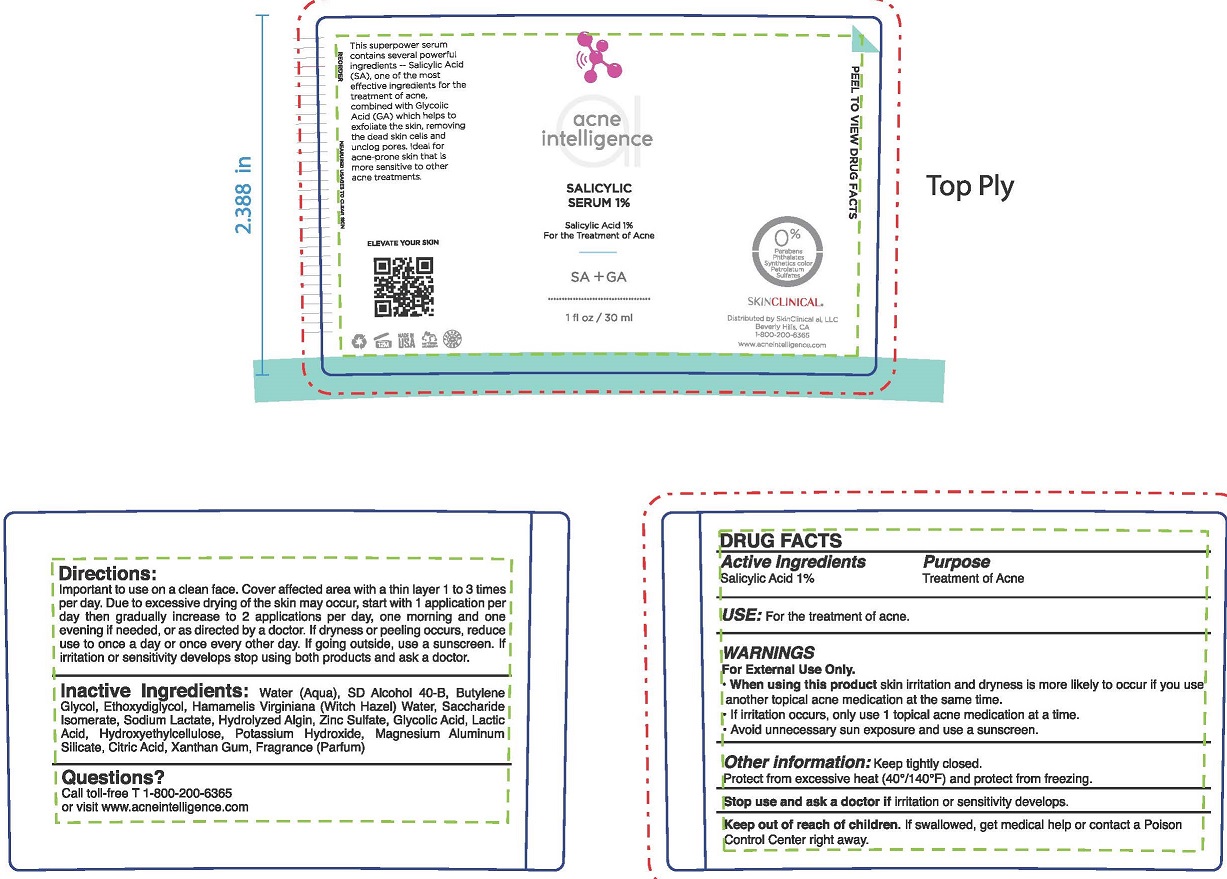 DRUG LABEL: SALICYLIC SERUM
NDC: 73110-101 | Form: GEL
Manufacturer: SkinClinical AI, LLC
Category: otc | Type: HUMAN OTC DRUG LABEL
Date: 20190503

ACTIVE INGREDIENTS: SALICYLIC ACID 1 g/100 mL
INACTIVE INGREDIENTS: BUTYLENE GLYCOL; DIETHYLENE GLYCOL MONOETHYL ETHER; SACCHARIDE ISOMERATE; SODIUM LACTATE; SODIUM ALGINATE; ZINC SULFATE; LACTIC ACID; POTASSIUM HYDROXIDE; XANTHAN GUM; GLYCOLIC ACID; MAGNESIUM ALUMINUM SILICATE; ANHYDROUS CITRIC ACID; WATER; ALCOHOL; WITCH HAZEL; HYDROXYETHYL CELLULOSE (100 MPA.S AT 2%)

SALICYLIC SERUM 1%

ACTIVE INGREDIENT

SALICYLIC ACID 1%

PURPOSE

TREATMENT OF ACNE

USE

For the treatment of acne.

WARNINGS

For External Use Only,
When using this product skin irritation and dryness is more likely to occur if you use another topical acne medication at the same time.

If irritation occurs, only use 1 topical acne medication at a time.
• Avoid unnecessary sun exposure and use a sunscreen.

OTHER INFORMATION

Keep tightly closed.
Protect from excessive heat (40°/140°F) and protect from freezing.

Stop use and ask a doctor if irritation or sensitivity develops.

Keep out of reach of children. If swallowed, get medical help or contact a Poison Control Center right away.

DIRECTIONS

Important to use on a clean face. Cover affected area with a thin layer 1 to 3 times per day. Due to excessive drying of the skin may occur, start with 1 application per day then gradually increase to 2 applications per day, one morning and one evening if needed, or as directed by a doctor. If dryness or peeling occurs, reduce use to once a day or once every other day. If going outside, use a sunscreen. If irritation or sensitivity develops stop using both products and ask a doctor.

INACTIVE INGREDIENTS

Water (Aqua), SD Alcohol 40-B, Butylene Glycol, Ethoxydiglycol, Hamamelis Virginiana (Witch Hazel) Water, Saccharide lsomerate, Sodium Lactate, Hydrolyzed Algin, Zinc Sulfate, Glycolic Acid, Lactic Acid, Hydroxyethylcellulose, Potassium Hydroxide, Magnesium Aluminum Silicate, Citric Acid, Xanthan Gum, Fragrance (Parfum)

QUESTIONS?

Call toll-free T 1-800-200-6365
or visit www.acneintelligence.com